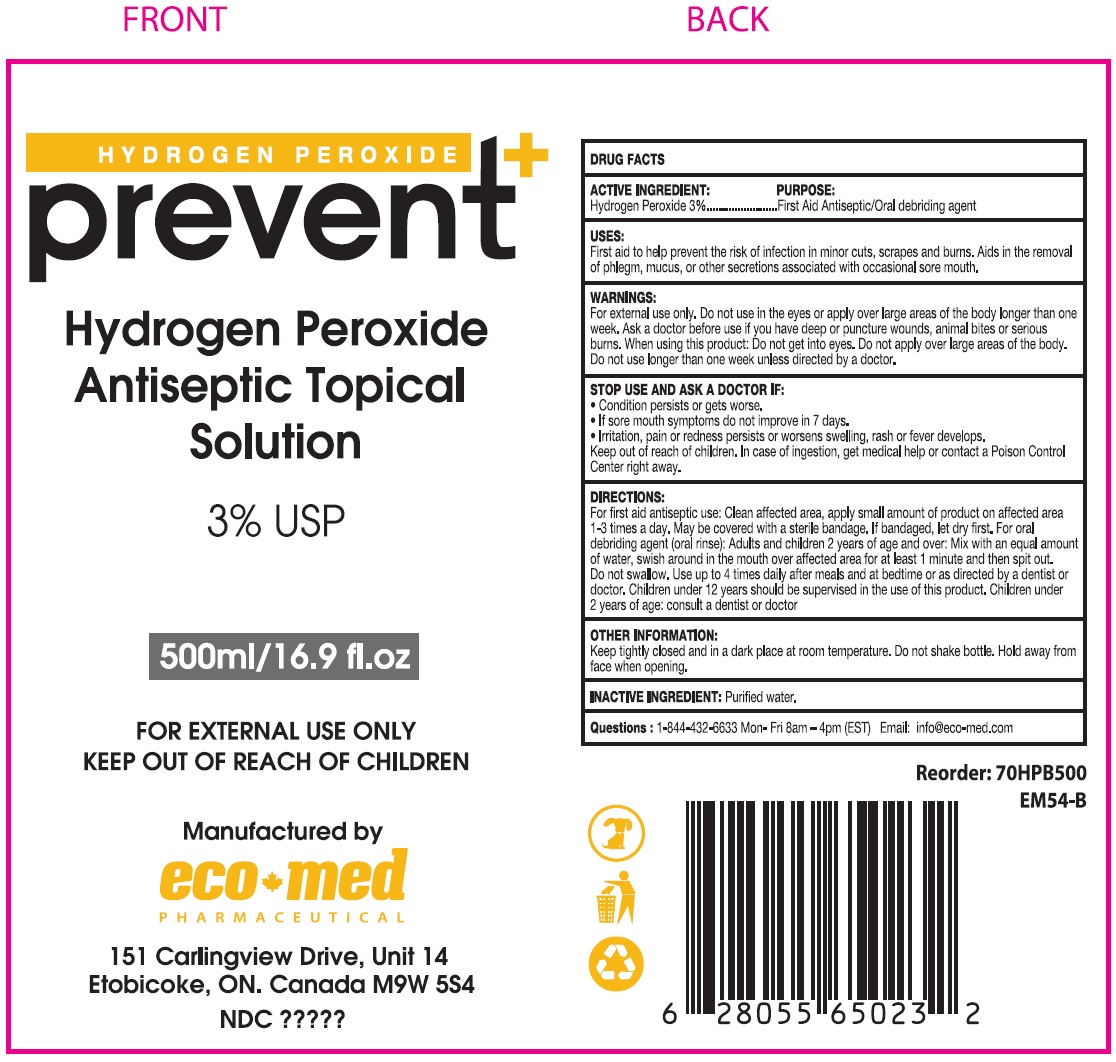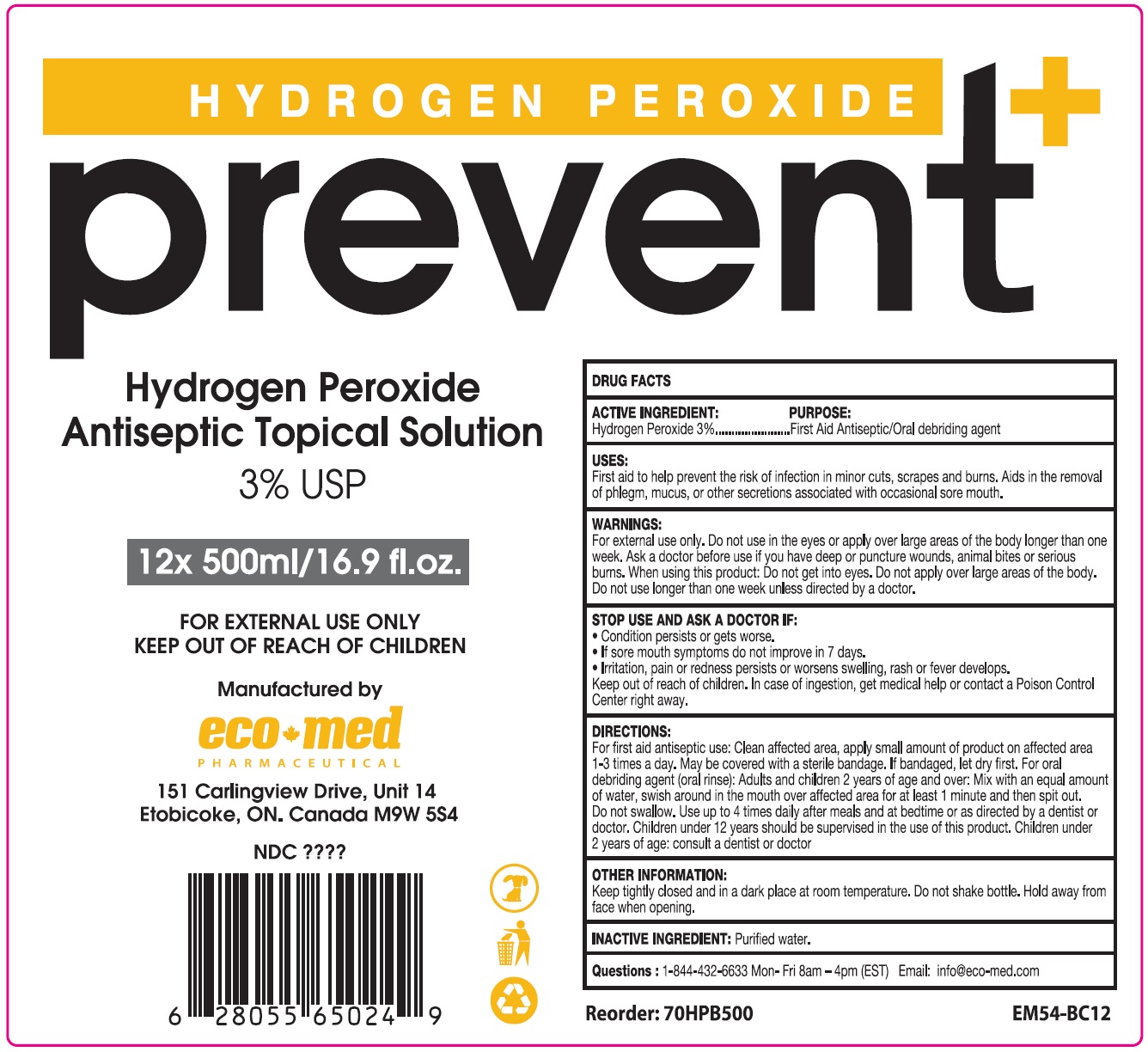 DRUG LABEL: Prevent Hydrogen Peroxide 3 Percent
NDC: 78835-008 | Form: LIQUID
Manufacturer: Eco-Med Pharmaceuticals, Inc.
Category: otc | Type: HUMAN OTC DRUG LABEL
Date: 20201029

ACTIVE INGREDIENTS: HYDROGEN PEROXIDE 0.03 mL/1 mL
INACTIVE INGREDIENTS: WATER

Prevent+ Hydrogen Peroxide 3% USP

ACTIVE INGREDIENT

Hydrogen Peroxide 3%

PURPOSE:

First Aid Antiseptic/Oral debriding agent

USES:

First aid to help prevent the risk of infection in minor cuts, scrapes and burns. Aids in the removal of phlegm, mucus, or other secretions associated with occasional sore mouth.

WARNINGS:

For external use only.

Do not use

in the eyes or apply over large areas of the body longer than one week. Ask a doctor before use if you have deep or puncture wounds, animal bites or serious burns.

When using this product:

Do not get into eyes. Do not apply over large areas of the body. Do not use longer than one week unless directed by a doctor .

STOP USE AND ASK A DOCTOR IF:

Condition persists or gets worse.

If sore mouth symptoms do not improve in 7 days.

Irritation, pain or redness persists or worsens swelling, rash or fever develops.

Keep out of reach of children.

In case of ingestion, get medical help or contact a Poison Control Center right away.

DIRECTIONS:

For first aid antiseptic use: Clean affected area, apply small amount of product on affected area 1-3 times a day. May be covered with a sterile bandage, If bandaged, let dry first, For oral debriding agent (oral rinse): Adults and children 2 years of age and over: Mix with an equal amount of water, swish around in the mouth over affected area for at least 1 minute and then spit out. Do not swallow. Use up to 4 times daily after meals and at bedtime or as directed by a dentist or doctor. Children under 12 years should be supervised in the use of this product. Children under 2 years of age: consult a dentist or doctor

OTHER INFORMATION:

Keep tightly closed and in a dark place at room temperature. Do not shake bottle. Hold away from face when opening.

INACTIVE INGREDIENT:

Purified water.

Questions:

1-844-432-6633 Mon- Fri 8am - 4 pm (EST) Email: info@eco-med.com